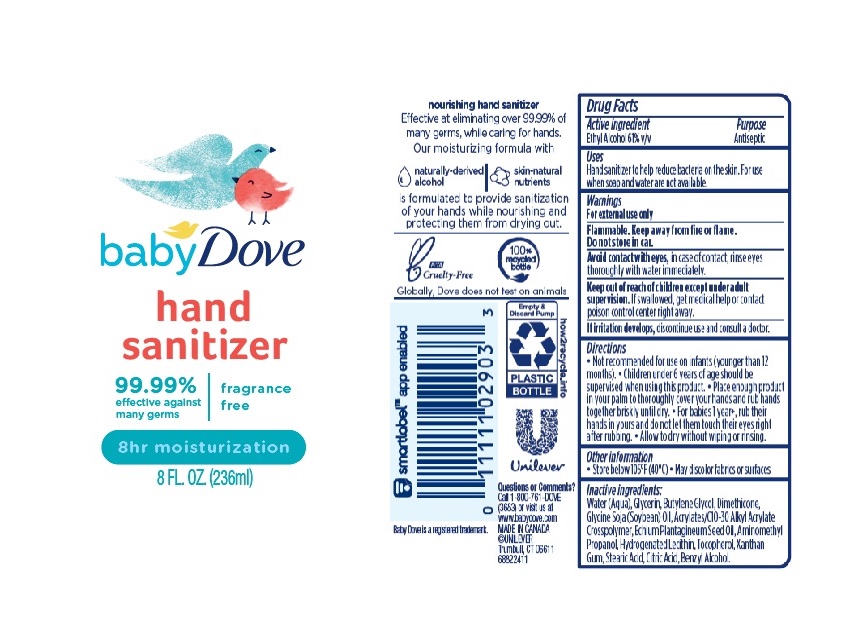 DRUG LABEL: Baby Dove
NDC: 64942-2036 | Form: GEL
Manufacturer: Conopco Inc. d/b/a/ Unilever
Category: otc | Type: HUMAN OTC DRUG LABEL
Date: 20241107

ACTIVE INGREDIENTS: ALCOHOL 610 mg/1 mL
INACTIVE INGREDIENTS: BENZYL ALCOHOL; BUTYLENE GLYCOL; WATER; GLYCERIN; DIMETHICONE; AMINOMETHYLPROPANOL; CARBOMER INTERPOLYMER TYPE A (55000 CPS); TOCOPHEROL; SOYBEAN OIL; HYDROGENATED SOYBEAN LECITHIN; XANTHAN GUM; CITRIC ACID MONOHYDRATE; ECHIUM PLANTAGINEUM SEED OIL; STEARIC ACID

Baby Dove 8h Moisturization Hand Sanitizer Fragrance Free

BABY DOVE 8H MOISTURIZATION HAND SANITIZER FRAGRANCE FREE - Ethyl Alcohol gel

Baby Dove 8h Moisturization Hand Sanitizer

Drug Facts

Active ingredient

Alcohol (61%)

Purpose

Antiseptic

Uses

Hand sanitizer to help reduce bacteria on the skin

Warnings

For external use only
Flammable. Keep away from fire or flame, Do not store in car.
Avoid contact with eyes, in case of contact, rinse eyes thoroughly with water immediately.

If irritation develps, discontinue use and consult a doctor.

Keep out of reach of children except under adult supervision.
If swallowed, get medical help or contact a poison control center right away.

Directions

• Not recommended for use on infants (younger than 12 months).
• Children under 6 years of age should be supervised when using this product.
• Place enough product in your palm to thoroughly cover your hands and rub hands togeter briskly until dry.
• for babies 1 year*, rub their hands in yours and do not let them touch their eyes right after rubbing
• Allow to dry without wiping or rinsing

Other information

Store below 105˚F (40˚C). May discolor fabrics or surfaces.

Inactive ingredients

Water (Aqua), Glycerin, Butylene Glycol, Dimethicone, Glycine Soja (Soybean) Oil, Acrylates/C10-30 Alkyl Acrylate Crosspolymer, Echium Plantagineum Seed Oil, Aminomethyl Propanol, Hydrogenated Lecithin, Tocopherol, Xanthan Gum, Stearic Acid, Citric Acid, Benzyl Alcohol

Questions or Comments?

Call 1-800-761-DOVE(3683) or visit us at www.babydove.com